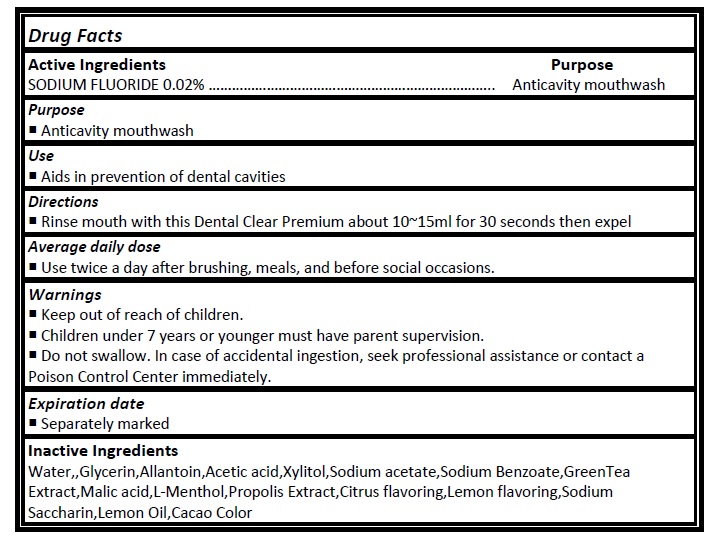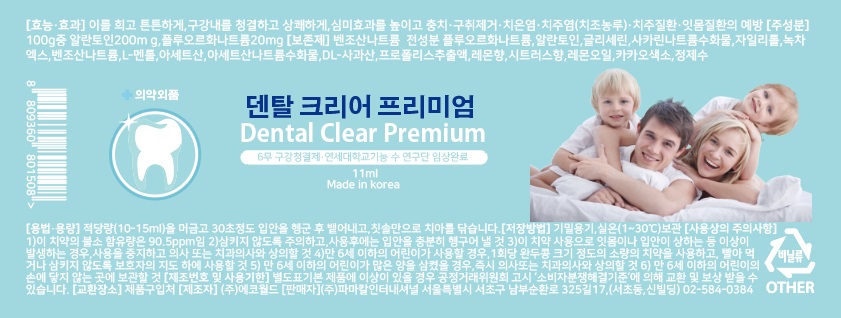 DRUG LABEL: Dental Clear Premium
NDC: 24765-127 | Form: RINSE
Manufacturer: Pharmacal-International. Co., Ltd.
Category: otc | Type: HUMAN OTC DRUG LABEL
Date: 20241025

ACTIVE INGREDIENTS: SODIUM FLUORIDE 0.2 mg/1 mL
INACTIVE INGREDIENTS: WATER; GLYCERIN; ALLANTOIN; ACETIC ACID; XYLITOL; SODIUM ACETATE; SODIUM BENZOATE; GREEN TEA LEAF; MALIC ACID; RACEMENTHOL; SACCHARIN SODIUM ANHYDROUS; LEMON OIL

Drug Facts

Active ingredient

Sodium Fluoride (0.02%)

Purpose

- Anticavity mouthwash

Use

- Aids in prevention of dental cavities

Directions

- Rinse mouth with this Dental Clear Premium about 10~15ml for 30 seconds then expel

Average daily dose

- Use twice a day after brushing, meals, and before social occasions.

Warnings

- Keep out of reach of children.
- Children under 7 years or younger must have parent supervision.
- Do not swallow. In case of accidental ingestion, seek professional assistance or contact a Poison Control Center immediately.

Inactive Ingredients

Water,,Glycerin,Allantoin,Acetic acid,Xylitol,Sodium acetate,Sodium Benzoate,GreenTea Extract,Malic acid,L-Menthol,Propolis Extract,Citrus flavoring,Lemon flavoring,Sodium Saccharin,Lemon Oil,Cacao Color